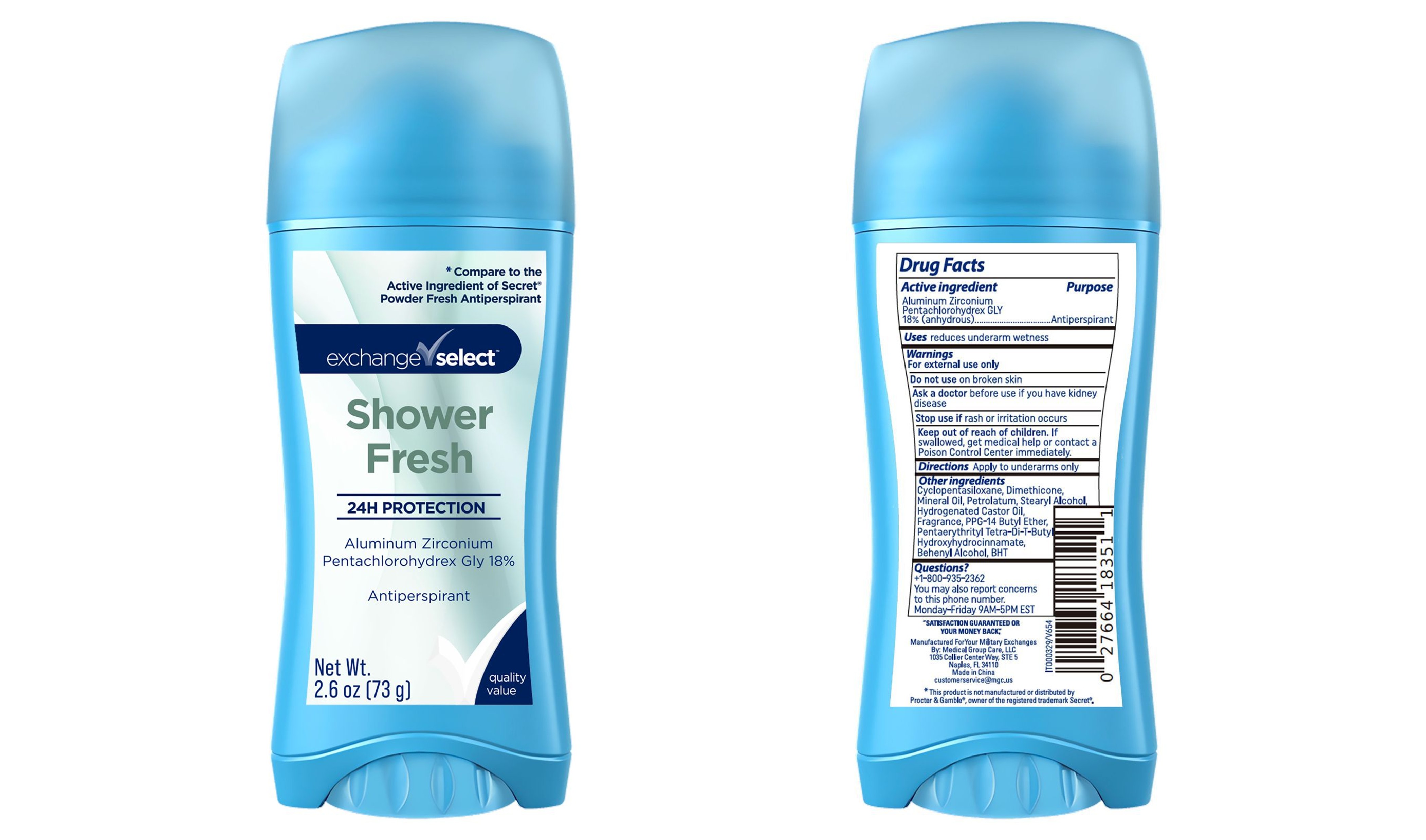 DRUG LABEL: Exchange Select Shower Fresh Deodorant
NDC: 85161-221 | Form: STICK
Manufacturer: Longway Technology(Guangzhou) Co., Ltd
Category: otc | Type: HUMAN OTC DRUG LABEL
Date: 20251118

ACTIVE INGREDIENTS: ALUMINUM ZIRCONIUM PENTACHLOROHYDREX GLY 180 mg/1 g
INACTIVE INGREDIENTS: CYCLOPENTASILOXANE; DIMETHICONE; MINERAL OIL; PETROLATUM; STEARYL ALCOHOL; HYDROGENATED CASTOR OIL; PPG-14 BUTYL ETHER; PENTAERYTHRITYL TETRA-DI-T-BUTYL HYDROXYHYDROCINNAMATE; BEHENYL ALCOHOL; BHT

Exchange Select Shower Fresh Deodorant

Drug Facts

Active ingredient

Aluminum Zirconium Pentachlorohydrex GLY 18% (Anhydrous)

Purpose

Antiperspirant

Use

reduces underarm wetness

Warnings

For external use only

Do not use

on broken skin

Ask a doctor

before use if you have kidney disease

Stop use if

rash or irritation occurs

Keep out of reach of children

If swallowed, get medical help or contact a Poison Control Center immediately.

Directions

Apply to underarms only

Inactive ingredients

Cyclopentasiloxane, Dimethicone, Mineral Oil, Petrolatum, Stearyl Alcohol, Hydrogenated Castor Oil, Fragrance, PPG-14 Butyl Ether, Pentaerythrityl Tetra-Di-T-Butyl Hydroxyhydrocinnamate, Behenyl Alcohol, BHT

Questions?

1-800-935-2362

You may also report concers to this phone
number
Monday-Friday, 9AM - 5PM EST.